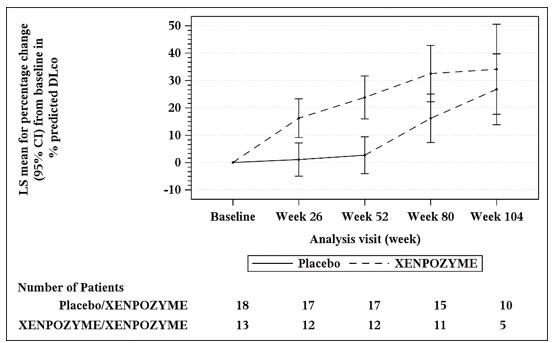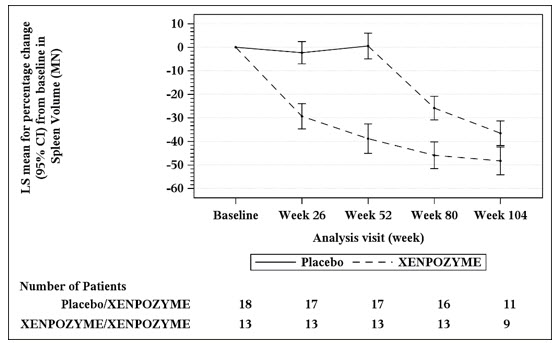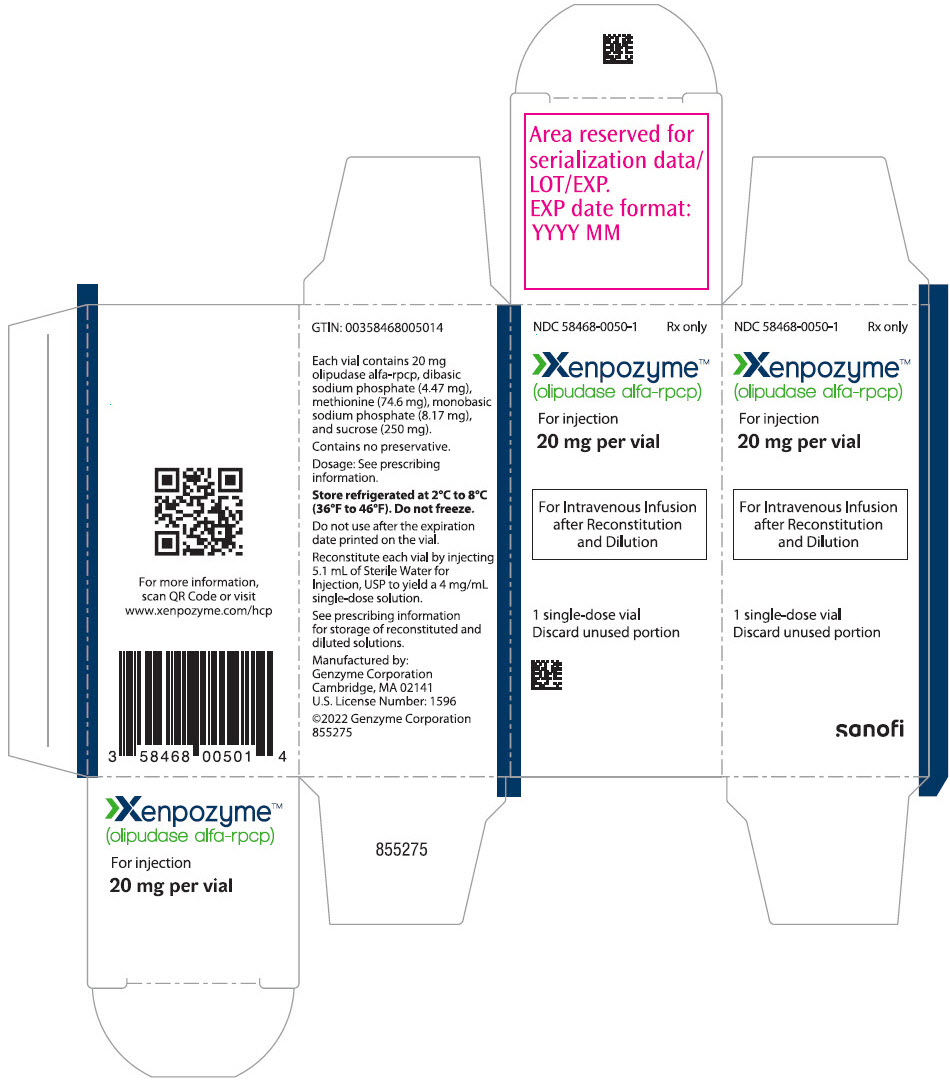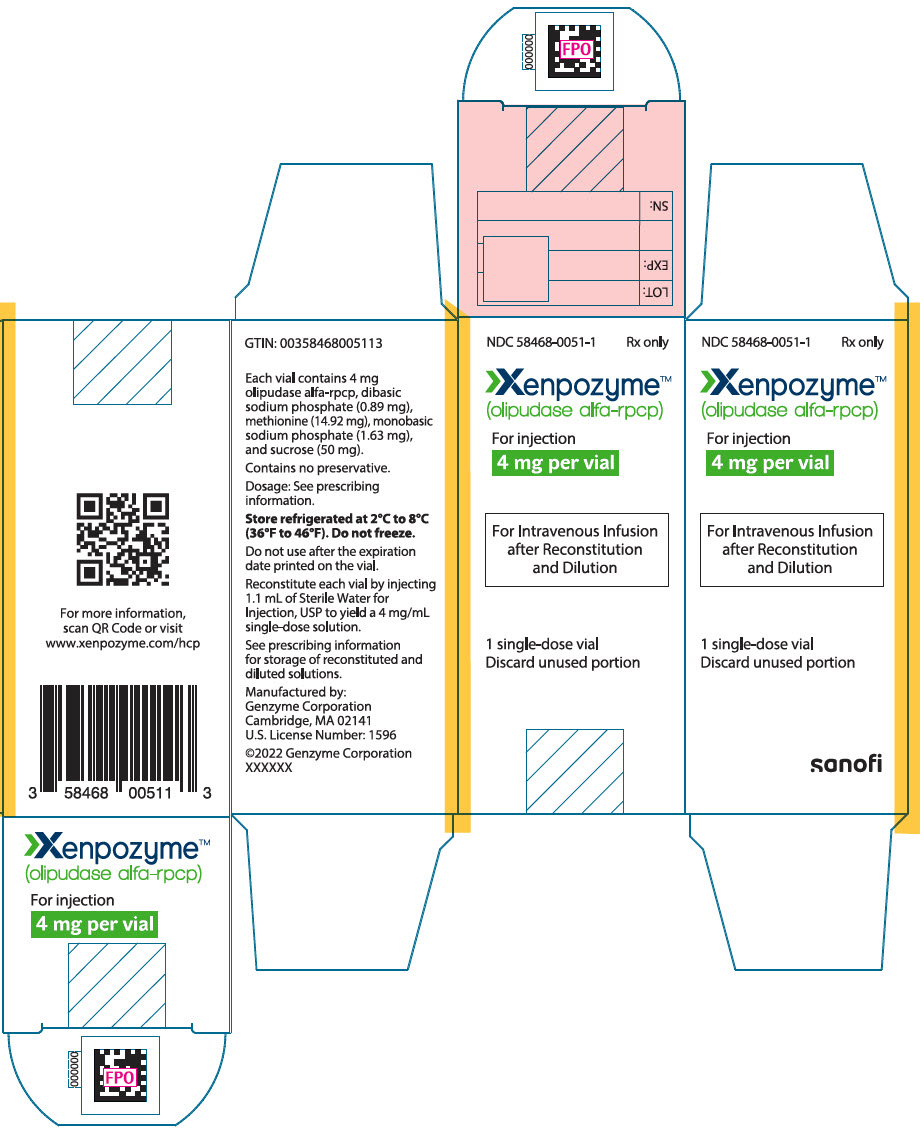 DRUG LABEL: XENPOZYME
NDC: 58468-0050 | Form: INJECTION, POWDER, LYOPHILIZED, FOR SOLUTION
Manufacturer: Genzyme Corporation
Category: prescription | Type: HUMAN PRESCRIPTION DRUG LABEL
Date: 20251211

ACTIVE INGREDIENTS: OLIPUDASE ALFA 20 mg/5.1 mL
INACTIVE INGREDIENTS: SODIUM PHOSPHATE, DIBASIC, HEPTAHYDRATE 4.47 mg/5.1 mL; SODIUM PHOSPHATE, MONOBASIC, MONOHYDRATE 8.17 mg/5.1 mL; SUCROSE 250 mg/5.1 mL; METHIONINE 74.6 mg/5.1 mL

HIGHLIGHTS OF PRESCRIBING INFORMATION

These highlights do not include all the information needed to use XENPOZYME safely and effectively. See full prescribing information for XENPOZYME.
XENPOZYME® (olipudase alfa-rpcp) for injection, for intravenous use
Initial U.S. Approval: 2022

WARNING: HYPERSENSITIVITY REACTIONS INCLUDING ANAPHYLAXIS

See full prescribing information for complete boxed warning.

Appropriate medical monitoring and support measures, including cardiopulmonary resuscitation equipment, should be readily available. If a severe hypersensitivity reaction occurs, discontinue XENPOZYME immediately and initiate appropriate medical treatment. (5.1)

RECENT MAJOR CHANGES

Dosage and Administration, Missed Doses (2.4) | 12/2024
Dosage and Administration, Administration Instructions (2.7) | 12/2024

1 INDICATIONS AND USAGE

XENPOZYME is a hydrolytic lysosomal sphingomyelin-specific enzyme indicated for treatment of non–central nervous system manifestations of acid sphingomyelinase deficiency (ASMD) in adult and pediatric patients. (1)

2 DOSAGE AND ADMINISTRATION

- See Full Prescribing Information for important recommendations prior to XENPOZYME treatment initiation. (2.1)
- Adults: Recommended starting dose is 0.1 mg/kg administered as an intravenous infusion. (2.2)
- Pediatrics: Recommended starting dose is 0.03 mg/kg administered as an intravenous infusion. (2.3)
- See Full Prescribing Information for the recommended dose escalation and maintenance dosage, dosage modifications to reduce the risk of adverse reactions, and preparation and administration instructions. (2.2, 2.3, 2.5, 2.6, 2.7)

3 DOSAGE FORMS AND STRENGTHS

For injection: 4 mg or 20 mg of olipudase alfa-rpcp as a lyophilized powder in a single-dose vial for reconstitution. (3)

4 CONTRAINDICATIONS

None. (4)

5 WARNINGS AND PRECAUTIONS

- Infusion-Associated Reactions (IARs): If severe IARs occur, discontinue XENPOZYME and initiate appropriate medical treatment. (5.2)
- Elevated Transaminases: Assess ALT and AST within one month prior to initiation of XENPOZYME, within 72 hours prior to any infusion during dose escalation, or prior to the next scheduled XENPOZYME infusion upon resuming treatment following a missed dose. (5.3)
- Risk of Fetal Malformations During Dosage Initiation or Escalation in Pregnancy: XENPOZYME dosage initiation or escalation, at any time during pregnancy, is not recommended as it may lead to elevated sphingomyelin metabolite levels that may increase the risk of fetal malformations. Advise females of reproductive potential to use effective contraception during treatment and for 14 days after the last dose if XENPOZYME is discontinued. (5.4, 8.1, 8.3)

6 ADVERSE REACTIONS

- Most common adverse reactions in adult patients (incidence ≥10%) are headache, cough, diarrhea, hypotension, and ocular hyperemia. (6.1)
- Most common adverse reactions in pediatric patients (incidence ≥20%) are pyrexia, cough, diarrhea, rhinitis, abdominal pain, vomiting, headache, urticaria, nausea, rash, arthralgia, pruritus, fatigue, and pharyngitis. (6.1)

To report SUSPECTED ADVERSE REACTIONS, contact Genzyme Corporation at 1-800-745-4447 or FDA at 1-800-FDA-1088 or www.fda.gov/medwatch.

FULL PRESCRIBING INFORMATION

WARNING: HYPERSENSITIVITY REACTIONS INCLUDING ANAPHYLAXIS

Patients treated with XENPOZYME have experienced life-threatening hypersensitivity reactions, including anaphylaxis. Appropriate medical monitoring and support measures, including cardiopulmonary resuscitation equipment, should be readily available during XENPOZYME administration. If a severe hypersensitivity reaction (e.g., anaphylaxis) occurs, discontinue XENPOZYME immediately and initiate appropriate medical treatment. In patients with severe hypersensitivity reactions, a desensitization procedure to XENPOZYME may be considered [see Warnings and Precautions (5.1)].

1 INDICATIONS AND USAGE

XENPOZYME is indicated for treatment of non–central nervous system manifestations of acid sphingomyelinase deficiency (ASMD) in adult and pediatric patients.

2 DOSAGE AND ADMINISTRATION

2.1 Important Recommendations Prior to XENPOZYME Treatment Initiation

Therapy with XENPOZYME should be directed in consultation with physicians knowledgeable in the management of ASMD. In order to avoid dosing errors including overdosage [see Overdosage (10)], follow all instructions for dosage and administration.

Laboratory Testing

Before initiating XENPOZYME:

- Obtain baseline transaminase (alanine aminotransferase [ALT] and aspartate aminotransferase [AST]) levels in all patients within 1 month prior to treatment initiation [see Warnings and Precautions (5.3)].
- Verify pregnancy status in females of reproductive potential [see Use in Specific Populations (8.1, 8.3)].

Premedication

Prior to XENPOZYME administration, consider premedicating with antihistamines, antipyretics, and/or corticosteroids [see Warnings and Precautions (5.1, 5.2)].

Medical Support

Appropriate medical support measures including cardiopulmonary resuscitation equipment should be readily available during XENPOZYME administration [see Warnings and Precautions (5.1)].

Weight-Based Dosing Information

The recommended adult and pediatric dosages of XENPOZYME for the dose escalation and maintenance phases [see Dosage and Administration (2.2, 2.3)] are based on body weight as follows for patients with a body mass index (BMI):

- Less than or equal to 30, the dosage is based on actual body weight (kg)
- Greater than 30, the dosage is based on adjusted body weight (kg). Calculate an adjusted body weight (kg) based on height in meters as described below:
  Adjusted body weight (kg) = (actual height in m)^2 × 30

2.2 Recommended Dosage in Adult Patients

Dose Escalation Phase

The recommended starting dose of XENPOZYME in adults is 0.1 mg/kg.

In order to reduce the risk of infusion-associated reactions or elevated transaminase levels, follow the dose escalation regimen in Table 1 [see Warnings and Precautions (5.1, 5.2, 5.3)].

Administer XENPOZYME via intravenous infusion every 2 weeks.

Table 1: XENPOZYME Dose Escalation Regimen for Adult Patients [Use actual body weight for patients with a BMI less than or equal to 30. For patients with a BMI greater than 30, calculate adjusted body weight (kg) = (actual height in m)^2 × 30 [see Dosage and Administration (2.1)].]
Adult Patients (18 years and older)
First dose (Day 1/Week 0) | 0.1 mg/kg
Second dose (Week 2) | 0.3 mg/kg
Third dose (Week 4) | 0.3 mg/kg
Fourth dose (Week 6) | 0.6 mg/kg
Fifth dose (Week 8) | 0.6 mg/kg
Sixth dose (Week 10) | 1 mg/kg
Seventh dose (Week 12) | 2 mg/kg
Eighth dose (Week 14) [The dose escalation phase includes the first 3 mg/kg dose.] | 3 mg/kg (recommended maintenance dose)

Maintenance Phase

The recommended maintenance dosage of XENPOZYME in adults is 3 mg/kg via intravenous infusion every 2 weeks.

2.3 Recommended Dosage in Pediatric Patients

Dose Escalation Phase

The recommended starting dose of XENPOZYME in pediatric patients is 0.03 mg/kg.

In order to reduce the risk of hypersensitivity and infusion-associated reactions or elevated liver enzyme elevations, follow the dose escalation regimen in Table 2 [see Warnings and Precautions (5.1, 5.2, 5.3)].

Administer XENPOZYME via intravenous infusion every 2 weeks.

Table 2: XENPOZYME Dose Escalation Regimen for Pediatric Patients [Use actual body weight for patients with a BMI less than or equal to 30. For patients with a BMI greater than 30, calculate adjusted body weight (kg) = (actual height in m)^2 × 30 [see Dosage and Administration (2.1)].]
Pediatric Patients (0 to 17 years)
First dose (Day 1/Week 0) | 0.03 mg/kg
Second dose (Week 2) | 0.1 mg/kg
Third dose (Week 4) | 0.3 mg/kg
Fourth dose (Week 6) | 0.3 mg/kg
Fifth dose (Week 8) | 0.6 mg/kg
Sixth dose (Week 10) | 0.6 mg/kg
Seventh dose (Week 12) | 1 mg/kg
Eighth dose (Week 14) | 2 mg/kg
Ninth dose (Week 16) [The dose escalation phase includes the first 3 mg/kg dose.] | 3 mg/kg (recommended maintenance dose)

Maintenance Phase

The recommended maintenance dosage of XENPOZYME in pediatric patients is 3 mg/kg via intravenous infusion every 2 weeks.

2.4 Missed Doses

A dose is considered missed when it is not administered within 3 days of the scheduled date. When a dose of XENPOZYME is missed, refer to Table 3. Follow the instructions in the "Escalation Phase" or "Maintenance Phase" depending on which phase the patient misses the dose.

Table 3: Dosing Recommendations for XENPOZYME Missed Doses [At scheduled infusion after a missed dose, if the dose administered is 0.3 or 0.6 mg/kg, administer that dose twice as per Table 1 and 2.]
Consecutive Missed Doses In: | Escalation Phase | Maintenance Phase
1 missed dose | - First dose after a missed dose: Administer last tolerated dose - Second and subsequent doses after missed dose: Resume dose escalation at next infusion according to Table 1 for adult patients or Table 2 for pediatric patients | First and subsequent doses after missed dose: Administer maintenance dose
2 consecutive missed doses | - First dose after missed dose: Administer 1 dose below last tolerated dose - Second and subsequent doses after missed dose: Resume dose escalation according to Table 1 for adults or Table 2 for pediatric patients | - First dose after missed dose: Administer 1 dose below the maintenance dose - Second and subsequent doses after missed dose: Resume the maintenance dose
3 or more consecutive missed doses | - For adult patients who have not completed the dose escalation phase: Reinitiate dose escalation regimen starting at 0.1 mg/kg and follow Table 1. - For pediatric patients who have not completed the dose escalation phase: Reinitiate dose escalation regimen starting at 0.03 mg/kg and follow Table 2. | First and subsequent doses after missed doses: Restart dosing at 0.3 mg/kg and follow Table 1 for adult patients or Table 2 for pediatric patients.; - For adult patients who have missed 3 or more consecutive doses in the mainenance phase during which sphingomyelin could have reaccumulated: The treating physician may consider resuming dosing at 0.1 mg/kg and dose escalate according to Table 1. - For pediatric patients who have missed 3 or more consecutive doses in the maintenance phase during which sphingomyelin could have reaccumulated: The treating physician may consider resuming dosing at 0.03 mg/kg and dose escalate according to Table 2.

2.5 Dosage and Administration Modifications and Monitoring

- In the event of a severe hypersensitivity reaction (e.g., anaphylaxis) or a severe infusion-associated reaction (IAR), immediately discontinue XENPOZYME administration and initiate appropriate medical treatment [see Warnings and Precautions (5.1, 5.2)].
- In the event of a mild to moderate hypersensitivity reaction or a mild to moderate IAR, consider temporarily holding or slowing the infusion rate, and/or reducing the XENPOZYME dose. If dose is reduced, re-escalate following dose escalation described in Tables 1 and 2 for adult and pediatric patients, respectively [see Warnings and Precautions (5.1, 5.2)].
- If transaminase levels are elevated above baseline and >2 times the ULN prior to the next scheduled administration, the XENPOZYME dose can be adjusted (prior dose repeated or reduced) or treatment can be temporarily withheld until the liver transaminases return to the patient's baseline value [see Warnings and Precautions (5.3)].

2.6 Preparation Instructions

Use aseptic technique during preparation. Reconstitute and dilute XENPOZYME in the following manner:

Reconstitution and Dilution Instructions

1. Determine the number of XENPOZYME vials to be reconstituted based on the calculated dose [see Dosage and Administration (2.2, 2.3)].
2. Remove XENPOZYME vials from refrigeration and set aside for approximately 20 to 30 minutes to allow vials to reach room temperature.
3. Reconstitute each vial with:
  - 1.1 mL of Sterile Water for Injection, USP into the 4 mg vial
  - 5.1 mL of Sterile Water for Injection, USP into the 20 mg vial
  by directing the diluent flow to the inside wall of the vial to avoid foaming.
4. Gently roll and tilt vial(s) to reconstitute XENPOZYME and avoid foaming. Each reconstituted vial will yield a 4 mg/mL clear, colorless solution.
5. Visually inspect the reconstituted solution in the vials for particulate matter and discoloration. The solution should be clear and colorless. Discard if the solution is discolored or if visible particulate matter is present.
6. Withdraw the required volume of XENPOZYME from the vial(s) and dilute the XENPOZYME solution for infusion with 0.9% Sodium Chloride Injection, USP in a syringe or infusion bag depending on the volume of infusion (see Table 4).
  - For patients who weigh less than 10 kg receiving 0.03 mg/kg and 0.1 mg/kg and patients who weigh between 10 to 20 kg receiving 0.03 mg/kg dose, the volume of infusion will vary to achieve a fixed final concentration of 0.1 mg/mL (see Table 4). Prepare the required dose diluted to a final concentration of 0.1 mg/mL in a syringe for infusion.
  - For all other patient weights and doses, the final concentration will vary to achieve a fixed total volume (see Table 4).
  - For total volume less than or equal to 20 mL prepare a syringe for infusion:
    - Inject the required volume of the reconstituted XENPOZYME solution (4 mg/mL) from step 3 slowly down the inside wall of the syringe.
    - Add slowly the quantity sufficient of 0.9% Sodium Chloride Injection, USP to obtain the required total infusion volume (avoid foaming within the syringe).
  - For a total volume of greater than or equal to 50 mL prepare an infusion bag:
    Add slowly the required volume of the reconstituted XENPOZYME solution (4 mg/mL) from step 3 into the appropriate size 0.9% Sodium Chloride Injection, USP infusion bag (avoid foaming within the bag) to achieve a fixed total volume per Table 4.
7. Gently invert the syringe or the infusion bag to mix. Do not shake. Because this is a protein solution, slight flocculation (described as thin translucent fibers) occurs occasionally after dilution.
8. Vials are for single dose only. Discard any unused solution.

Storage and Handling of the Reconstituted and Diluted Solutions

- If the reconstituted XENPOZYME vials are not used immediately, store refrigerated at 2°C to 8°C (36°F to 46°F) for up to 24 hours or at controlled room temperature at 20°C to 25°C (68°F to 77°F) for up to 6 hours. Discard the unused XENPOZYME reconstituted solution after 24 hours if stored refrigerated or 6 hours if stored at controlled room temperature.
- If the diluted solution is not used immediately, refrigerate the diluted solution at 2°C to 8°C (36°F to 46°F) for up to 24 hours or store at room temperature at 20°C to 25°C (68°F to 77°F) for up to 12 hours (inclusive of infusion time), or discard.
- Do not freeze.

Table 4: XENPOZYME Infusion Volumes for Pediatric and Adult Patients Based on Body Weight [Use actual or adjusted body weight per patient BMI. Refer to section 2. [see Dosage and Administration (2.2, 2.3)].]
 | Pediatric Patients (0 to 17 years) |  |  | Adult patients (18 years and older)
 | Body Weight ≥2 kg and <10 kg | Body Weight ≥10 kg and <20 kg | Body Weight ≥20 kg | Body Weight ≥20 kg
XENPOZYME Dose | Total Infusion Volume
0.03 mg/kg | Actual volume will vary [Volume will vary to achieve a final concentration of 0.1 mg/mL] (0.6 mL to 3 mL) | Actual volume will vary (3 mL to 6 mL) | 5 mL | NA
0.1 mg/kg | Actual volume will vary (2 mL to 10 mL) | 5 mL | 10 mL | 20 mL
0.3 mg/kg | 5 mL | 10 mL | 20 mL | 100 mL
0.6 mg/kg | 10 mL | 20 mL | 50 mL | 100 mL
1 mg/kg | 20 mL | 50 mL | 100 mL | 100 mL
2 mg/kg | 50 mL | 75 mL | 200 mL | 100 mL
3 mg/kg | 50 mL | 100 mL | 250 mL | 100 mL

2.7 Administration Instructions

1. Prior to administration, inspect the syringe or infusion bag for foaming. If foaming is present, let foam dissipate before administering XENPOZYME.
2. Use a low-protein binding, 0.2 micron, in-line filter during administration. The following materials can be used: polyolefin or polyvinylchloride (PVC) with DEHP for infusion bags, polypropylene for syringes, polyurethane or PVC DEHP-free for infusion sets and polyethersulfone or polytetrafluoroethylene for in-line filters.
3. Infuse XENPOZYME using the infusion rates described in Table 5 and Table 6. In absence of infusion-associated reactions, increase infusion rate per the steps of infusion as indicated (+/- 5 minutes). Each step of infusion will last for 20 minutes with the exception of the final step which should last until completion of the infusion volume.
4. At the end of the infusion, flush the infusion line with 0.9% Sodium Chloride Injection, USP using the same infusion rate as the one used for the last part of the infusion.
5. Do not infuse XENPOZYME in the same intravenous line with other products.

Table 5: XENPOZYME Infusion Rates for Adult Patients
Dose | Infusion Rate
 | step 1 | step 2 | step 3 | step 4
0.1 mg/kg | 20 mL/hour | 60 mL/hour | NA | NA
0.3 to 3 mg/kg | 3.33 mL/hour | 10 mL/hour | 20 mL/hour | 33.33 mL/hour
NA: Not applicable.
Start infusion at step 1 and in absence of infusion-associated reaction increase infusion rate sequentially per the steps of infusion.

Table 6: XENPOZYME Infusion Rates for Pediatric Patients
Dose | Infusion rate
Dose | step 1 | step 2 | step 3 | step 4
0.03 mg/kg | 0.1 mg/kg/hour for the full length of the infusion | NA | NA | NA
0.1 mg/kg | 0.1 mg/kg/hour | 0.3 mg/kg/hour | NA | NA
0.3 mg/kg | 0.1 mg/kg/hour | 0.3 mg/kg/hour | 0.6 mg/kg/hour | NA
0.6 mg/kg | 0.1 mg/kg/hour | 0.3 mg/kg/hour | 0.6 mg/kg/hour | 1 mg/kg/hour
1 mg/kg | 0.1 mg/kg/hour | 0.3 mg/kg/hour | 0.6 mg/kg/hour | 1 mg/kg/hour
2 mg/kg | 0.1 mg/kg/hour | 0.3 mg/kg/hour | 0.6 mg/kg/hour | 1 mg/kg/hour
3 mg/kg | 0.1 mg/kg/hour | 0.3 mg/kg/hour | 0.6 mg/kg/hour | 1 mg/kg/hour
NA: Not applicable.
Start infusion at step 1 and in absence of infusion-associated reactions increase infusion rate sequentially per the steps of infusion.

Home Infusion

Home administration under the supervision of a healthcare provider may be considered for patients on maintenance dose [see Dosage and Administration (2.2, 2.3)] and who are tolerating their infusion well. The decision to have patients moved to home infusion should be made after evaluation and recommendation by a physician.

The dose and infusion rate used in the home setting should remain the same as were used in the supervised clinical setting and should not be changed without supervision of a physician. In case of missed dose(s) or delayed infusion, contact a physician as subsequent infusions may occur in a supervised clinical setting.

3 DOSAGE FORMS AND STRENGTHS

For injection: 4 mg or 20 mg of olipudase alfa-rpcp as a sterile, white to off white lyophilized powder in a single-dose vial for reconstitution.

4 CONTRAINDICATIONS

None.

5 WARNINGS AND PRECAUTIONS

5.1 Hypersensitivity Reactions Including Anaphylaxis

Life-threatening hypersensitivity reactions, including anaphylaxis, have been reported in olipudase alfa-treated patients. One 18-month-old XENPOZYME-treated patient experienced an anaphylactic reaction during the sixth infusion in the dose escalation period in Trial 2 [see Adverse Reactions (6.1)]. Additionally, a 16-month-old patient with ASMD type A, treated with a version of olipudase alfa manufactured from a different process, experienced two anaphylactic reactions during the fifth and sixth infusions in the dose escalation period; the patient received an immune tolerance induction therapy prior to treatment. In both of these pediatric patients with anaphylaxis, anti-olipudase alfa-rpcp IgE (IgE ADA) and IgG (IgG ADA) antibodies were detected [see Adverse Reactions (6.1) and Clinical Pharmacology (12.6)].

Hypersensitivity reactions that were mild to moderate in severity occurred in 10 (33%) XENPOZYME-treated adult patients and 4 (50%) XENPOZYME-treated pediatric patients in clinical trials. Hypersensitivity reactions in adults included urticaria, pruritus, erythema, rash, rash erythematous, eczema, angioedema, and erythema nodosum. Hypersensitivity reactions in pediatric patients included urticaria, pruritus, rash, erythema, and localized edema [see Adverse Reactions (6)].

Prior to XENPOZYME administration, consider premedicating with antihistamines, antipyretics, and/or corticosteroids. Appropriate medical monitoring and support measures, including cardiopulmonary resuscitation equipment, should be readily available during XENPOZYME administration.

- If a severe hypersensitivity reaction (e.g., anaphylaxis) occurs, discontinue XENPOZYME immediately and initiate appropriate medical treatment. Consider the risks and benefits of re-administering XENPOZYME following a severe hypersensitivity reaction (including anaphylaxis). One patient has been rechallenged using slower infusion rates at a dosage lower than the recommended dosage. In patients with a severe hypersensitivity reaction, a tailored desensitization procedure to XENPOZYME may be considered. If the decision is made to readminister XENPOZYME, ensure the patient tolerates the infusion. If the patient tolerates the infusion, the dosage (dose and/or the rate) may be increased to reach the recommended dosage.
  - Consider testing for IgE ADA in XENPOZYME-treated patients who experienced severe hypersensitivity reactions, including anaphylaxis [see Adverse Reactions (6.1)]. Testing for antibodies against olipudase alfa-rpcp are available through Genzyme Corporation (at 1-800-745-4447). Consider other clinical laboratory testing such as serum tryptase and complement activation in patients who experience anaphylaxis.
- If a mild or moderate hypersensitivity reaction occurs, consider temporarily holding the infusion, slowing the infusion rate, and/or reducing the XENPOZYME dose [see Dosage and Administration (2.5)].

5.2 Infusion-Associated Reactions

IARs occurred in approximately 75% of pediatric and 50% of adult XENPOZYME-treated patients in the clinical trials; a severe IAR occurred in one (12.5%) of the pediatric patients. The most frequent IARs in:

- ≥10% of adult patients were headache, pruritus, vomiting, and urticaria
- >20% of pediatric patients were urticaria, erythema, headache, nausea, pyrexia, and vomiting

Acute phase reaction (APR), an acute inflammatory response accompanied by elevations in inflammatory serum protein concentrations, was observed in one XENPOZYME-treated adult and one XENPOZYME-treated pediatric patient. Most of the APRs occurred at 48 hours post infusion during the dose escalation period. Elevations of C-reactive protein, calcitonin, and IL-6, and reduction of serum iron were observed. The most common clinical symptoms associated with APRs were pyrexia, vomiting, and diarrhea. Acute phase reactions were managed similar to other IARs. In the postmarketing setting, 24 hours after receiving XENPOZYME at a higher than recommended initial dose, a 2-year-old male patient with ASMD, experienced fever, respiratory distress, hypotension, and death [see Overdosage (10)].

Prior to XENPOZYME administration, consider pre-medicating with antihistamines, antipyretics, and/or corticosteroids to reduce the risk of infusion-associated reactions (IARs). However, IARs may still occur in patients after receiving pre-treatment. Follow the dose escalation regimen to minimize IARs [see Dosage & Administration (2.2 & 2.3)].

- If a severe IAR occurs, discontinue XENPOZYME immediately and initiate appropriate medical treatment. Consider the risks and benefits of re-administering XENPOZYME following a severe IAR. One patient has been rechallenged using slower infusion rates at a dosage lower than the recommended dosage. If the patient tolerates the infusion, the dosage (dose and/or the rate) may be increased to reach the recommended dosage.
- If a mild or moderate IAR occurs, consider temporarily holding the infusion, slowing the infusion rate, and/or reducing the XENPOZYME dosage [see Dosage and Administration (2.5)].

5.3 Elevated Transaminase Levels

XENPOZYME may be associated with elevated transaminases (ALT, AST, or both) within 24 to 48 hours after infusion. Elevated transaminase levels were reported in 4 (13%) XENPOZYME-treated adults and 1 (13%) XENPOZYME-treated pediatric patient during the dose escalation phase in clinical trials. At the time of the next scheduled infusion, these elevated transaminase levels generally returned to levels observed prior to the XENPOZYME infusion [see Adverse Reactions (6.1)].

To manage the risk of elevated transaminase levels, assess ALT and AST within one month prior to initiation of XENPOZYME, within 72 hours prior to any infusion during dose escalation, which includes the first 3 mg/kg dose outlined in Tables 1 and 2, or prior to the next scheduled XENPOZYME infusion upon resuming treatment following a missed dose.

If either the baseline or pre-infusion transaminase level (during the dose escalation phase) is >2 times the ULN, repeat transaminase levels within 72 hours after the end of the infusion. If the pre-infusion transaminase levels are elevated above baseline and >2 times the ULN prior to the next scheduled administration, the XENPOZYME dose can be reduced (repeat prior lower dose or reduce the dose) or XENPOZYME can be temporarily withheld until the liver transaminases return to the patient's baseline value.

Upon reaching the recommended maintenance dose, transaminase testing is recommended to be continued as part of routine clinical management of ASMD.

5.4 Risk of Fetal Malformations During Dosage Initiation or Escalation in Pregnancy

There is no evidence that olipudase alfa-rpcp crosses the human placenta. However, published literature reports that early embryonic exposure to a metabolite of sphingomyelin (ceramide) or the S1P receptor modulator fingolimod can produce exencephaly in chicks and mice, respectively. In animal reproduction studies, exencephaly, a neural tube defect occurring in the first trimester of pregnancy, was observed in mouse fetuses at exposures less than the exposure at the maximum recommended human dose of olipudase alfa-rpcp.

XENPOZYME dosage initiation or escalation, at any time during pregnancy, is not recommended as it may lead to elevated sphingomyelin metabolite levels that may increase the risk of fetal malformations [see Use in Specific Population (8.1), Clinical Pharmacology (12.2)]. The decision to continue or discontinue XENPOZYME maintenance dosing in pregnancy should consider the female's need for XENPOZYME, the potential drug-related risks to the fetus, and the potential adverse outcomes from untreated maternal ASMD disease.

Verify the pregnancy status in females of reproductive potential prior to initiating XENPOZYME treatment. Advise females of reproductive potential to use effective contraception during treatment and for 14 days after the last dose if XENPOZYME is discontinued [see Use in Specific Populations (8.3)].

6 ADVERSE REACTIONS

The following clinically significant adverse reactions are described elsewhere in the labeling:

- Hypersensitivity Reactions Including Anaphylaxis [see Warnings and Precautions (5.1)]
- Infusion-Associated Reactions (IARs) [see Warnings and Precautions (5.2)]
- Elevated Transaminase Levels [see Warnings and Precautions (5.3)]

6.1 Clinical Trials Experience

Because clinical trials are conducted under widely varying conditions, adverse reaction rates observed in the clinical trials of a drug cannot be directly compared to rates in the clinical trials of another drug and may not reflect the rates observed in practice.

The pooled safety analysis from 3 clinical trials included a total of 38 XENPOZYME-treated patients (30 adult and 8 pediatric patients) with age range from 1.5 to 59 years old receiving intravenous doses up to 3 mg/kg every 2 weeks [see Clinical Studies (14)]. The median exposure duration was 2.5 years (range: 0.4 to 3.7 years) in adult patients and 2.7 years (range: 2.5 to 3.2 years) in pediatric patients.

Serious adverse reactions of anaphylactic reaction were reported in 2 (25%) XENPOZYME-treated pediatric patients.

Most frequently reported adverse drug reactions in adults (incidence ≥10%) were headache, cough, diarrhea, hypotension, and ocular hyperemia.

Most frequently reported adverse drug reactions in pediatric patients (incidence ≥20%) were pyrexia, cough, diarrhea, rhinitis, abdominal pain, vomiting, headache, urticaria, nausea, rash, arthralgia, pruritus, fatigue, and pharyngitis.

Adult patients with ASMD type B and type A/B (Trial 1)

In Trial 1, 13 adult patients received XENPOZYME once every 2 weeks for 52 weeks (primary analysis period (PAP)) at dosages escalating from 0.1 mg/kg to a target dose of 3 mg/kg [see Clinical Studies (14.2)].

Adverse reactions that occurred in at least 7% of XENPOZYME-treated adult patients during the PAP are described in Table 7.

Table 7: Adverse Reactions Occurring at >7% in Adult Patients with ASMD During the 52-Week Primary Analysis Period in Trial 1
Adverse Reaction | XENPOZYME N=13 | Placebo N=18
Headache | 7 (54%) | 8 (44%)
Cough | 4 (31%) | 2 (11%)
Diarrhea | 2 (15%) | 2 (11%)
Hypotension | 2 (15%) | 2 (11%)
Ocular hyperemia | 2 (15%) | 1 (6%)
Erythema | 1 (8%) | 1 (6%)
Asthenia | 1 (8%) | 1 (6%)
Pharyngitis | 1 (8%) | 1 (6%)
Dyspnea | 1 (8%) | 0
Urticaria | 1 (8%) | 0
Papule | 1 (8%) | 0
Myalgia | 1 (8%) | 0
Throat irritation | 1 (8%) | 0
C-reactive protein abnormal | 1 (8%) | 0

Pediatric Patients with ASMD type B and type A/B (Trial 2 and Trial 3)

In Trial 2, 8 pediatric patients less than or equal to 17 years of age received XENPOZYME intravenously once every 2 weeks for 64 weeks [see Clinical Studies (14.3)]. After 64 weeks, all pediatric patients entered into Trial 3.

Adverse reactions that occurred in at least 13% of pediatric patients are described in Table 8.

Table 8: Adverse Reactions Occurring at ≥13% in XENPOZYME-Treated Pediatric Patients with ASMD in Trial 2 [Duration of treatment in Trial 2 was 64 weeks. All patients continued into Trial 3.] and Trial 3 for an Overall Observation Period of 2.5 to 3.2 Years
Adverse Reactions | XENPOZYME N=8
Pyrexia | 8 (100%)
Cough | 6 (75%)
Diarrhea | 6 (75%)
Rhinitis | 6 (75%)
Abdominal pain | 5 (63%)
Vomiting | 4 (50%)
Headache | 4 (50%)
Urticaria | 4 (50%)
Nausea | 3 (38%)
Rash | 3 (38%)
Arthralgia | 3 (38%)
Pruritus | 2 (25%)
Fatigue | 2 (25%)
Pharyngitis | 2 (25%)
C-reactive protein increased | 1 (13%)
Hypotension | 1 (13%)
Anaphylactic reaction | 1 (13%)
Hypersensitivity | 1 (13%)
Infusion site swelling | 1 (13%)
Tachycardia | 1 (13%)
Pharyngeal swelling | 1 (13%)
Abdominal pain includes abdominal pain and abdominal pain upper
Fatigue includes fatigue and asthenia
Rash includes rash and erythema

Treatment related serious adverse reactions, hypersensitivity reactions including anaphylaxis, and IARs occurred within 24 hours of infusion and were observed in a higher percentage of pediatric patients than in adult patients.

Laboratory Adverse Reaction

Elevated transaminase levels ranging from 3 times to 14 times the upper limit of normal (ULN) were reported in 4 (13%) adults and 1 (13%) pediatric patient during the XENPOZYME dose escalation phase in clinical trials.

Immunogenicity: Antidrug Antibody-Associated Adverse Reactions

In Trial 1, infusion-associated reactions (including hypersensitivity reactions) occurred in a higher percentage in XENPOZYME-treated patients who developed IgG ADA compared to those who did not develop IgG ADA (73% versus 44%) [see Clinical Pharmacology (12.6) and Clinical Studies (14.2)].

In Trial 2, one XENPOZYME-treated pediatric patient (18-months old) experienced an anaphylactic reaction during the sixth infusion and developed IgE ADA and the highest IgG ADA titers (ADA peak titer 1,600) of the patients in this trial. After treatment discontinuation, XENPOZYME was resumed four months later using a diluted drug solution and a desensitization procedure.

One pediatric patient (16-months old) with ASMD type A, treated with a version of olipudase alfa manufactured from a different process, experienced anaphylactic reactions (both during the fifth and sixth infusions) and developed IgG ADA (highest titer 1,600) and IgE ADA [see Warnings and Precautions (5.1)].

8 USE IN SPECIFIC POPULATIONS

8.1 Pregnancy

Risk Summary

Based on findings from animal reproduction studies, XENPOZYME may cause embryo-fetal harm when administered to a pregnant female. XENPOZYME dosage initiation or escalation, at any time during pregnancy, is not recommended as it may lead to elevated sphingomyelin metabolite levels that may increase the risk of fetal malformations (see Data), [see Clinical Pharmacology (12.2)]. However, the decision to continue or discontinue XENPOZYME maintenance dosing in pregnancy should consider the female's need for XENPOZYME, the potential drug-related risks to the fetus, and the potential adverse outcomes from untreated maternal ASMD disease.

In an embryo-fetal toxicity study in pregnant mice, a rare malformation (exencephaly) was observed in offspring at an exposure less than the exposure at the maximum recommended human dose (MRHD) of olipudase alfa-rpcp (see Data).

There are no available data on XENPOZYME use in pregnant females to evaluate for a drug associated risk of major birth defects, miscarriage, or other adverse maternal or fetal outcomes. Advise the pregnant female of the potential risk to the fetus.

The background risk of major birth defects and miscarriage for the indicated population is unknown. All pregnancies have a background risk of birth defect, miscarriage, or other adverse outcomes. In the U.S. general population, the estimated background risk of major birth defects and miscarriage in clinically recognized pregnancies is 2% to 4% and 15% to 20%, respectively.

Data

Animal Data

In an embryo-fetal development study in pregnant mice, olipudase alfa-rpcp was administered intravenously at doses of 3, 10, or 30 mg/kg daily from gestation day (GD) 6 through GD 15. Exencephaly was observed in 1 litter at each of the 10 and 30 mg/kg dose groups (2 and 3 fetuses, respectively). These data are consistent with published literature reports that brief embryonic exposures to sphingomyelin metabolites or a sphingosine-1-phosphate (S1P) receptor modulator produced neural tube defects, including exencephaly, in chicks and mice.

The developmental No Observed Adverse Effect Level (NOAEL) is 3 mg/kg. The AUC associated with this dose is 0.14-fold the clinical exposure at the MRHD. The developmental Lowest-Observed-Adverse-Effect Level (LOAEL), 10 mg/kg, is also associated with an exposure that is less than the clinical exposure at the MRHD.

In an embryo-fetal development study in pregnant rabbits, olipudase alfa-rpcp was administered intravenously at doses of 3, 10, or 30 mg/kg daily from GD 6 through GD 19. There was no maternal or developmental toxicity. The developmental NOAEL was 30 mg/kg; the AUC0–24 at this dose is approximately 10.5-fold the exposure at the MRHD.

In a study of pre- and postnatal development in mice, olipudase alfa-rpcp was administered intravenously every other day from GD 6 through GD 18; then resumed every other day after parturition, from Lactation Day (LD) 1 through LD 19. Olipudase alfa-rpcp did not induce any effect on maternal reproductive function or on developmental and reproductive parameters of male and female offspring. Therefore, the maternal and developmental NOAELs are 30 mg/kg. Exposures at this dose, based on the embryo-fetal development study, were estimated to be approximately 1.5-fold the MRHD of olipudase alfa-rpcp.

8.2 Lactation

Risk Summary

There are no data on the presence of olipudase alfa-rpcp in human milk, the effects on the breastfed infant, or the effects on milk production. Olipudase alfa-rpcp is present in animal milk. (see Data). When a drug is present in animal milk, it is likely that the drug will be present in human milk. The developmental and health benefits of breastfeeding should be considered along with the mother's clinical need for XENPOZYME and any potential adverse effects on the breastfed infant from XENPOZYME or from the underlying maternal condition.

Data

Olipudase alfa-rpcp was administered as a single intravenous dose (3 mg/kg) to lactating CD1 mice on post-partum day 7. Milk was not evaluated until post-partum day 9, at which time concentrations of olipudase alfa-rpcp detected were approximately 1.3% the estimated maximal maternal plasma concentration.

8.3 Females and Males of Reproductive Potential

XENPOZYME may cause embryo-fetal harm when administered during the first trimester of pregnancy [see Use in Specific Populations (8.1)].

Pregnancy Testing

Verify the pregnancy status in females of reproductive potential prior to initiating XENPOZYME.

Contraception

Females

Advise females of reproductive potential to use effective contraception during treatment and for 14 days after the last dose if XENPOZYME is discontinued.

8.4 Pediatric Use

The safety and effectiveness of XENPOZYME for the treatment of non-central nervous system manifestations of acid sphingomyelinase deficiency (ASMD) have been established in pediatric patients down to birth.

Use of XENPOZYME for this indication is supported by evidence from an adequate, and well-controlled trial (Trial 1) in adults with supportive efficacy, safety, and tolerability data in pediatric patients (Trial 2 and Trial 3) [see Adverse Reactions (6.1) and Clinical Studies (14.2, 14.3, 14.4)].

Compared to adults, a higher percentage of pediatric patients experienced treatment related serious adverse reactions, anaphylaxis, hypersensitivity reactions, and IARs that occurred within 24 hours of infusion [see Adverse Reactions (6.1)]. Two pediatric patients, an 18 month old receiving XENPOZYME and a 16 month old with ASMD type A that received a version of olipudase alfa manufactured from a different process developed anaphylaxis [see Warnings and Precautions (5.1)].

8.5 Geriatric Use

Of the total number of XENPOZYME-treated adult patients in these trials, 1 (3%) was 65 to 74 years of age, and none were 75 years of age and older [see Clinical Studies (14)].

Clinical trials of XENPOZYME did not include sufficient numbers of patients 65 years of age and older to determine whether they respond differently from younger adult patients.

10 OVERDOSAGE

Cases of overdosage with XENPOZYME have been reported in pediatric patients during dose escalation. Some patients experienced serious adverse reactions including death within 24 hours of initial dose [see Warnings and Precautions (5.2)]. The clinical findings included fever, hypotension, gastrointestinal bleeding, marked elevation in liver tests, metabolic acidosis, respiratory failure, and vomiting.

There is no known specific antidote for XENPOZYME overdosage. In the event of overdosage, immediately stop the infusion, and monitor the patient closely in a hospital setting for the development of hypersensitivity reactions and IARs including acute phase reactions. For the management of adverse reactions, see Warnings and Precautions (5.1, 5.2, 5.3) and Adverse Reactions (6.1).

11 DESCRIPTION

Olipudase alfa-rpcp is a hydrolytic lysosomal sphingomyelin-specific enzyme consisting of 570 amino acids produced in a Chinese hamster ovary cell line by recombinant DNA technology. The molecular weight of olipudase alfa-rpcp is approximately 76 kDa.

XENPOZYME (olipudase alfa-rpcp) for injection is supplied as a sterile, preservative-free, white to off-white lyophilized powder for reconstitution and dilution to be administered via intravenous infusion. XENPOZYME is supplied in single-dose vials.

Each 4 mg vial contains 4 mg olipudase alfa-rpcp, dibasic sodium phosphate (0.89 mg), methionine (14.92 mg), monobasic sodium phosphate (1.63 mg), and sucrose (50 mg). After reconstitution with 1.1 mL of Sterile Water for Injection, USP, the final concentration is 4 mg/mL [see Dosage and Administration (2.6)].

Each 20 mg vial contains 20 mg olipudase alfa-rpcp, dibasic sodium phosphate (4.47 mg), methionine (74.6 mg), monobasic sodium phosphate (8.17 mg), and sucrose (250 mg). After reconstitution with 5.1 mL of Sterile Water for Injection, USP, the final concentration is 4 mg/mL [see Dosage and Administration (2.6)].

The pH is 6.5 after reconstitution.

12 CLINICAL PHARMACOLOGY

12.1 Mechanism of Action

ASMD is a lysosomal storage disease that results from reduced activity of the enzyme acid sphingomyelinase (ASM), caused by pathogenic variants in the sphingomyelin phosphodiesterase 1 gene. ASM degrades sphingomyelin to ceramide and phosphocholine. The deficiency of ASM causes an intra-lysosomal accumulation of sphingomyelin (as well as cholesterol and other cell membrane lipids) in various tissues. XENPOZYME provides an exogenous source of ASM.

XENPOZYME is not expected to cross the blood-brain barrier or modulate the CNS manifestations of ASMD.

12.2 Pharmacodynamics

Plasma Ceramide Levels

Ceramide is elevated in plasma of adult and pediatric patients with ASMD. Plasma ceramide levels showed a transient increase after each administration (post infusion) of XENPOZYME. In the dose escalation phase, plasma ceramide levels were substantially increased compared to the baseline level. Plasma ceramide levels gradually decreased following repeated administration of XENPOZYME and the pre-infusion levels were generally lower than the baseline level during the maintenance phase of treatment.

- In adult patients with ASMD in Trial 1 [see Clinical Studies (14.2)], the mean (standard deviation, SD) pre-infusion plasma ceramide concentration was 3.7 (1.4) mg/L at baseline and decreased to 2.2 (0.6) mg/L at Week 52 following treatment with XENPOZYME.
- In pediatric patients with ASMD in Trial 2 [see Clinical Studies (14.3)], the mean (SD) pre-infusion plasma ceramide concentration was 4.7 (0.9) mg/L at baseline and decreased to 1.8 (0.3) mg/L at Week 52 following treatment with XENPOZYME.

Plasma Lysosphingomyelin Levels

Lysosphingomyelin is substantially elevated in plasma of adult and pediatric patients with ASMD. Plasma lysosphingomyelin levels decreased after repeated administration of XENPOZYME.

- In adult patients with ASMD in Trial 1 [see Clinical Studies (14.2)], the mean (SD) pre-infusion plasma lysosphingomyelin concentration was 379 (204) mcg/L at baseline and decreased to 99 (118) mcg/L at Week 52 following treatment with XENPOZYME.
- In pediatric patients with ASMD in Trial 2 [see Clinical Studies (14.3)], the mean (SD) pre-infusion plasma lysosphingomyelin concentration was 625 (339) mcg/L at baseline and decreased to 80 (47) mcg/L at Week 52 following treatment with XENPOZYME.

Liver Sphingomyelin Content

In adult patients, the liver sphingomyelin content, as assessed by histopathology, decreased from baseline to Week 52 in the XENPOZYME treatment group compared to an increase in the placebo group.

12.3 Pharmacokinetics

In adult patients with ASMD, the mean (SD) maximum plasma olipudase alfa-rpcp concentration (Cmax) and area under the concentration-time curve (AUC) at steady state were 30 (5) mcg/mL and 607 (120) mcg∙h/mL, respectively, at the recommended maintenance dose of 3 mg/kg administered once every 2 weeks. Olipudase alfa-rpcp Cmax and AUC increase proportionally over a dose range of 0.1 to 3 mg/kg (0.03 to 1 times the approved recommended maintenance dose).

Distribution

The mean (SD) volume of distribution of olipudase alfa-rpcp was 13 (2) L in adult patients with ASMD.

Elimination

The mean (SD) clearance of olipudase alfa-rpcp was 0.33 (0.07) L/h and the mean half-life (t1/2) ranged from 32 to 38 hours in adult patients with ASMD.

Metabolism

The metabolic pathway of olipudase alfa-rpcp has not been characterized. Olipudase alfa-rpcp is expected to be metabolized into small peptides and amino acids via catabolic pathways.

Specific Populations

Pediatric Patients

In pediatric patients (1.5 to 17.5 years of age) with ASMD, the mean (SD) Cmax was 24.3 (2.8) mcg/mL and the mean (SD) AUC was 449 (70) mcg∙h/mL at the recommended maintenance dose of 3 mg/kg administered once every 2 weeks.

12.6 Immunogenicity

The observed incidence of anti-drug antibodies is highly dependent on the sensitivity and specificity of the assay. Differences in assay methods preclude meaningful comparisons of the incidence of anti-drug antibodies in the studies described below with the incidence of anti-drug antibodies in other studies, including those of olipudase alfa-rpcp or of other olipudase alfa products.

Following 0.4 to 3.7 years of XENPOZYME treatment in Trial 1 [see Clinical Studies (14.2)], 9 out of 30 (30%) XENPOZYME-treated adult patients with ASMD developed anti-olipudase alfa-rpcp IgG antibodies (referred to as IgG ADA). The median time to seroconversion from first XENPOZYME infusion was approximately 8 weeks. One out of these 9 (11%) adult patients had neutralizing antibodies (NAb) that inhibited the olipudase alfa-rpcp enzyme activity. None of these 9 patients had NAb that inhibit the cellular uptake of olipudase alfa-rpcp.

Following 2.5 to 3.2 years of XENPOZYME treatment in Trial 2 and 3 [see Clinical Studies (14.3)], 6 out of 8 (75%) XENPOZYME-treated pediatric patients with ASMD developed IgG ADA. The median time to seroconversion from first XENPOZYME infusion was 10 weeks. One out of the 6 (17%) pediatric patients developed NAb that inhibited olipudase alfa-rpcp enzyme activity. None of these 6 patients had NAb that inhibited the cellular uptake of olipudase alfa-rpcp.

Infusion-associated reactions (including hypersensitivity reactions) occurred in a higher percentage in XENPOZYME-treated patients who developed ADA compared to those who did not develop ADA [see Warnings and Precautions (5.1) and Adverse Reactions (6.1)].

There was no identified clinically significant effect of ADA on pharmacokinetics of XENPOZYME.

13 NONCLINICAL TOXICOLOGY

13.1 Carcinogenesis, Mutagenesis, Impairment of Fertility

Carcinogenesis

Studies to evaluate the carcinogenic potential of olipudase alfa-rpcp have not been conducted.

Mutagenesis

Studies to evaluate the mutagenic potential of olipudase alfa-rpcp have not been conducted.

Impairment of Fertility

Intravenous administration of olipudase alfa-rpcp every other day at doses up to 30 mg/kg had no adverse effects in a combined study of fertility in male and female mice. Exposures at this dose, based on the embryo-fetal development study, were estimated to be approximately 1.5-fold those of the MRHD of olipudase alfa-rpcp.

13.2 Animal Toxicology and/or Pharmacology

In acid sphingomyelinase knockout (ASMKO) mice (a disease model of ASMD), mortality was observed after a single dose ≥10 mg/kg administered as an IV bolus injection. Observations (lethargy, coolness to touch, and unwillingness to move), combined with the adrenal hemorrhage, suggested that hypotensive shock may be the cause of death. These findings were accompanied by necrosis and apoptosis in the liver and adrenal gland, elevations of ceramide, sphingosine and sphingosine 1-phosphate in the serum, catabolites of accumulated sphingomyelin as well as elevations in the serum concentrations of inflammatory mediators, such as cytokines and acute phase proteins.

In ASMKO mice, a dose-dependent reduction in heart rate accompanied by a decrease in motor activity and followed by a slow decline in blood pressure was noted after a single IV administration at 3, 10, and 20 mg/kg. After 2 doses of olipudase alfa-rpcp at 3 and 10 mg/kg to ASMKO mice, a slight decline in heart rate was noted following the second administration.

Repeated dose studies in adult ASMKO mice show that administration of olipudase alfa-rpcp via a dose escalation regimen, (3 mg/kg administered IV every other day, followed by a single IV dose of 20 mg/kg 3 days later) did not result in toxicity. The lack of adverse findings in BALB/c, C57BL/6 mice, rats, dogs, and monkeys at comparable olipudase alfa-rpcp doses suggested that the dose-related toxicity observed in ASMKO mice may be due to the rate and amount of substrate degradation.

14 CLINICAL STUDIES

14.1 Overview of Clinical Trials

The efficacy of XENPOZYME for the treatment of non–central nervous system manifestations of acid sphingomyelinase deficiency (ASMD) has been evaluated in 3 clinical trials involving a total of 61 patients with ASMD:

- Trial 1 in adult patients (NCT02004691),
- Trial 2 in pediatric patients (NCT02292654), and
- Trial 3 a long-term trial in pediatric patients (NCT02004704).

14.2 Clinical Trial in Adult Patients with ASMD

Trial 1 was a multicenter, randomized, double-blinded, placebo-controlled, repeat-dose phase II/III trial in adult patients with ASMD (clinical diagnosis consistent with ASMD type B and A/B). In this trial, patients received either XENPOZYME or placebo. Treatment was administered in both groups as an intravenous infusion once every 2 weeks. XENPOZYME was dosed as follows: 0.1 mg/kg (Day 1, Week 0), 0.3 mg/kg (Weeks 2 and 4), 0.6 mg/kg (Weeks 6 and 8), 1 mg/kg (Week 10), 2 mg/kg (Week 12), and then a maintenance dose of 3 mg/kg (Week 14 onwards). The trial was divided into 2 consecutive periods: a randomized placebo-controlled, double-blinded primary analysis period (PAP) which lasted to Week 52, followed by an extension treatment period (ETP) for up to 4 years. Patients randomized to the placebo arm in the PAP crossed over to receive XENPOZYME treatment in the ETP to reach the targeted dose of 3 mg/kg, while patients in the original XENPOZYME arm continued treatment.

Patients enrolled in the trial had a diffusion capacity of the lungs for carbon monoxide (DLco) ≤70% of the predicted normal value and a spleen volume ≥6 multiples of normal (MN) measured by magnetic resonance imaging (MRI). The trial population included 87% White, 7% Asian, and 7% other; for ethnicity, 32% identified as Hispanic/Latino, 65% as non-Hispanic/Latino, and 3% were not reported.

Five males and 13 females with a median age of 34 years (range: 18 to 66) were included in the placebo arm and 8 males and 5 females with a median age of 34 years (range: 20 to 59) were included in the XENPOZYME arm. The XENPOZYME and placebo groups included 1 patient (8%) and 2 patients (11%) with mild renal impairment (60 mL/minute ≤ creatinine clearance <90 mL/minute), respectively. There were no patients with moderate or severe renal impairment.

Key efficacy endpoints included assessment of % predicted DLco, spleen volume, liver volume, and platelet count.

At Week 52 during the PAP, an increase of 21% in the mean percent change in % predicted DLco was observed in the XENPOZYME-treated patients compared to the placebo-treated patients (Table 9). A reduction in spleen volume of 39% was observed in the XENPOZYME-treated patients compared to the placebo-treated patients. The changes in % predicted DLco and spleen volume were noted at Week 26 of treatment, the first post-dose endpoint assessment (Figures 1 and 2).

A decrease in mean liver volume and an increase in mean platelet count were noted in the XENPOZYME-treated patients compared to the placebo-treated patients at Week 52 (Table 9).

Table 9: Observed Value and Percentage Change from Baseline to Week 52 in Key Endpoints in Adult Patients with ASMD Type B, A/B on XENPOZYME or Placebo (Trial 1)
 | Placebo | XENPOZYME | Difference [95% CI]
DLco
n | 18 | 13
Mean % predicted DLco at baseline (SD) | 48.5 (10.8) | 49.1 (9.7) | NA
n | 17 | 12
Mean % predicted DLco at Week 52 (SD) | 49.9 (11.1) | 59.4 (9.6) | NA
n | 17 | 12
LS Mean Percent change in % predicted DLco at Week 52 (SE) | 3.0 (3.3) | 23.9 (3.8) | 20.9 (5.0) [p value = 0.0003;] [10.6, 31.2]
Spleen volume
n | 18 | 13
Mean Spleen Volume (MN) at baseline (SD) | 11.2 (3.8) | 11.5 (4.7) | NA
n | 17 | 13
Mean Spleen Volume (MN) at Week 52 (SD) | 11.2 (4.2) | 7.2 (3.9) | NA
n | 17 | 13
LS Mean Percent change in Spleen Volume (in MN) at Week 52 (SE) | 0.5 (2.62) | -38.9 (3.0) | -39.4 (4.0) [p value <0.0001;] [-47.6, -31.2]
Liver volume
n | 18 | 13
Mean Liver Volume (MN) at baseline (SD) | 1.6 (0.5) | 1.4 (0.3) | NA
n | 17 | 12
Mean Liver Volume (MN) at Week 52 (SD) | 1.6 (0.5) | 1.0 (0.2) | NA
n | 17 | 12
LS Mean Percent change in Liver Volume from baseline to Week 52 (SE) | -1.8 (2.7) | -26.5 (3.2) | -24.7 (4.2) [-33.4, -16.1]
Platelet count
n | 18 | 13
Mean Platelet Count (10^9/L) at baseline (SD) | 115.6 (36.3) | 109.3 (30.6) | NA
n | 16 | 13
Mean Platelet Count (10^9/L) at Week 52 (SD) | 120.2 (43.2) | 126.4 (29.0) | NA
n | 16 | 13
LS Mean Percent change in Platelet Count from baseline to Week 52 (SE) | 2.7 (4.5) | 18.3 (5.0) | +15.6 (6.7) [p value= 0.0280] [1.8, 29.4]
Nominal p value:

Seventeen of 18 patients previously receiving placebo and 13 of 13 patients previously treated with XENPOZYME for 52 weeks (in the PAP) started or continued treatment with XENPOZYME, respectively, for up to 4 years. At Week 104, patients initially randomized to placebo had received XENPOZYME for 52 weeks and demonstrated the following LS mean (SE) percent changes in clinical parameters from baseline (before first administration of XENPOZYME): increase in % predicted DLco was 26.8% (6.2) (Figure 1); reduction in spleen volume (MN) was 36.5% (2.5) (Figure 2); reduction in liver volume (MN) was 29.5 (2.6); and increase in platelet count was 19.5 (6.7).

Patients in the previous XENPOZYME group demonstrated improvement from baseline to Week 104 in the following parameters: LS mean (SE) percent increase in % predicted DLco was 34.1% (7.9) (Figure 1); LS mean (SE) percent reduction in spleen volume (MN) was 48.3 (2.9) (Figure 2); LS mean (SE) percent reduction in liver volume (MN) was 31.7 (2.9); LS mean (SE) percent increase in platelet count was 24.0 (8.2).

Figure 1: Plot of the LS Means (95% CI) of the Percentage Change in DLco (% predicted) from Baseline to Week 104 in Adult Patients with ASMD (Trial 1)

The vertical bars represent the 95% CIs for the LS means.

The LS means and 95% CIs are based on a mixed model for repeated measures approach, using data up to Week 104. Patients in placebo/XENPOZYME group received placebo by Week 52 and switched to XENPOZYME thereafter.

Figure 2: Plot of the LS Means (95% CI) of the Percentage Change in Spleen Volume (MN) from Baseline to Week 104 in Patients with ASMD (Trial 1)

The vertical bars represent the 95% CIs for the LS means.

The LS means and 95% CIs are based on a mixed model for repeated measures approach, using data up to Week 104. Patients in placebo/XENPOZYME group received placebo by Week 52 and switched to XENPOZYME thereafter.

14.3 Clinical Trial in Pediatric Patients with ASMD

Trial 2 was a multi-center, open-label, repeated-dose trial of XENPOZYME administered intravenously once every 2 weeks (via infusion) for 64 weeks in pediatric patients aged <18 years with a clinical diagnosis consistent with ASMD type B and A/B. Exploratory efficacy endpoints related to organomegaly, pulmonary and liver functions, and linear growth were evaluated at Week 52. XENPOZYME was dosed as follows: 0.03 mg/kg (Day 1, Week 0), 0.1 mg/kg (Weeks 2), 0.3 mg/kg (Weeks 4 and 6), 0.6 mg/kg (Week 8 and 10), 1 mg/kg (Week 12), 2 mg/kg (Week 14), and then a maintenance dose of 3 mg/kg (Week 16 onwards).

In Trial 2, 8 patients (7 patients from 2 to <12 years old, and 1 patient <2 years old) received an initial dose of 0.03 mg/kg XENPOZYME and all but one completed the dose escalation up to the maintenance dose of 3 mg/kg within 22 weeks. All patients were White and of non-Hispanic/Latino ethnicity.

Patients enrolled in the trial had a spleen volume ≥5 MN measured by MRI. Age of patients treated with XENPOZYME ranged from 1 to 10 years old, with both sexes equally represented.

Treatment with XENPOZYME resulted in improvements in mean percent change in % predicted DLco, spleen and liver volumes, platelet counts, and linear growth progression (as measured by height Z-scores) at Week 52 as compared to baseline (Table 10).

Table 10: Efficacy Results in XENPOZYME-Treated Pediatric Patients with ASMD (Trial 2)
 | Baseline Values | Week 52 Values
 | (n=3) | (n=3)
Mean % predicted DLco (SD) | 48.5 (8.1) | 70.9 (13.7)
LS Mean Percent change in % predicted DLco* (SE) |  | 45.9 (22.7)
95% CI |  | -12.5, 104.3
 | (n=8) | (n=8)
Mean Spleen Volume (MN) (SD) | 18.3 (5.6) | 9.50 (2.4)
LS Mean Percent change in Spleen Volume (in MN) (SE) |  | -46.7 (3.6)
95% CI |  | -55.5, -37.9
 | (n=8) | (n=8)
Mean Liver Volume (MN) (SD) | 2.5 (0.5) | 1.6 (0.3)
LS Mean Percent change in Liver Volume (in MN) (SE) |  | -38.1 (2.9)
95% CI |  | -44.1, -32.0
 | (n=8) | (n=7)
Mean Platelet Count (10^9/L) (SD) | 136.7 (33.2) | 184.5 (54.2)
LS Mean Percent change in Platelet Count (SE) |  | 37.6 (13.7)
95% CI |  | 8.5, 66.7
 | (n=8) | (n=7)
Mean height Z-scores (SD) | -1.9 (0.8) | -1.5 (1.0)
LS Mean Change in height Z-scores (SE) |  | 0.5 (0.1)
95% CI |  | 0.2, 0.8

14.4 Extension Trial in ASMD Pediatric Patients

The 8 pediatric patients 2 to <12 years of age from Trial 2 continued treatment in an open label long term trial (Trial 3) and were treated with XENPOZYME for 2.5 to 3.2 years.

Efficacy analyses showed continued improvements in the 3 patients evaluated for % predicted DLco, 6 patients evaluated for platelet counts, and all 8 patients evaluated for spleen and liver volumes, compared to baseline, during the additional 6 months extension. In addition, the height Z-score increased by 1.3 from baseline when evaluated through 24 months of XENPOZYME treatment. Bone age, as assessed by hand x-ray, was delayed by a mean of 26.4 months at baseline in the 7 pediatric patients enrolled in Trial 2 with a bone age measured at Month 24 in Trial 3. The bone age improved to within a mean of 12 months of the chronological age when assessed at Month 24 in these 7 patients.

16 HOW SUPPLIED/STORAGE AND HANDLING

How Supplied

XENPOZYME (olipudase alfa-rpcp) for injection is supplied as a sterile white to off-white lyophilized powder for reconstitution in a single-dose vial. XENPOZYME does not contain any preservatives.

XENPOZYME is available supplied as:

- Carton containing one 20 mg single-dose vial (NDC 58468-0050-1)
- Carton containing one 4 mg single-dose vial (NDC 58468-0051-1)

Storage and Handling

Store refrigerated at 2°C to 8°C (36°F to 46°F). Do not freeze.

For storage of reconstituted and diluted solution [see Dosage and Administration (2.6)].

17 PATIENT COUNSELING INFORMATION

Hypersensitivity Reactions (Including Anaphylaxis) and Infusion-Associated Reactions (IARs)

Advise the patient and caregiver that reactions related to the infusion may occur during and after XENPOZYME treatment, including life-threatening hypersensitivity reactions, anaphylaxis, and IARs. Inform the patient and/or caregiver of the signs and symptoms of hypersensitivity reactions and IARs and to seek immediate medical care should signs and symptoms occur [see Warnings and Precautions (5.1, 5.2)].

Embryo-Fetal Toxicity

XENPOZYME may cause embryo-fetal harm. Advise the pregnant female and females of reproductive potential of the potential risk to the fetus. Advise a female patient and caregiver to inform their healthcare provider of a known or suspected pregnancy [see Use in Specific Populations (8.1)].

Advise a female of reproductive potential to use effective contraception during treatment and for 14 days after the last dose if XENPOZYME is discontinued [see Use in Specific Populations (8.1, 8.3)].

Manufactured by:
Genzyme Corporation
450 Water Street
Cambridge, MA 02141
U.S. License Number: 1596

©2024 Sanofi. All rights reserved. XENPOZYME is a registered trademark of Genzyme Corporation.

PRINCIPAL DISPLAY PANEL - 20 mg Vial Carton

NDC 58468-0050-1
Rx only

Xenpozyme™
(olipudase alfa-rpcp)

For injection

20 mg per vial

For Intravenous Infusion
after Reconstitution
and Dilution

1 single-dose vial
Discard unused portion

PRINCIPAL DISPLAY PANEL - 4 mg Vial Carton

NDC 58468-0051-1
Rx only

Xenpozyme™
(olipudase alfa-rpcp)

For injection

4 mg per vial

For Intravenous Infusion
after Reconstitution
and Dilution

1 single-dose vial
Discard unused portion